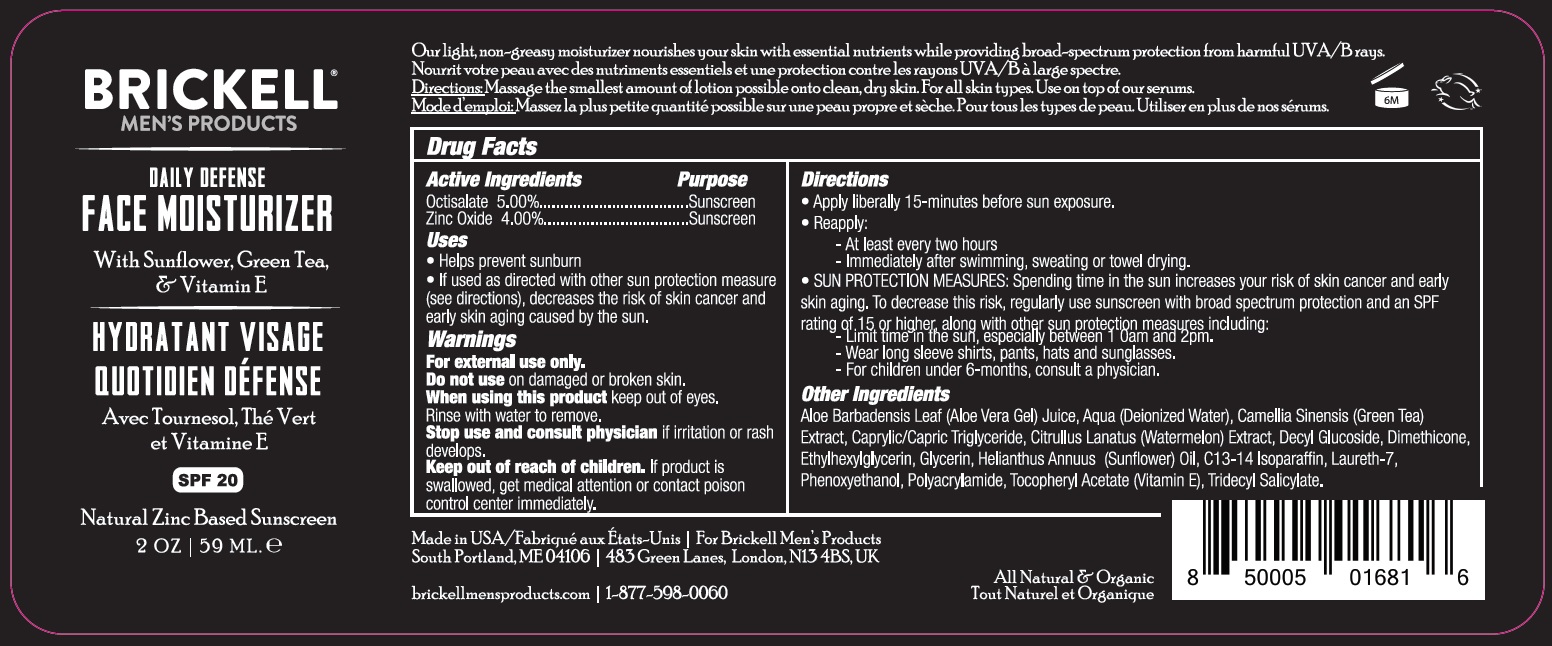 DRUG LABEL: BRICKELL Daily Defense Face Moisturizer SPF-20
NDC: 82247-225 | Form: CREAM
Manufacturer: BRICKELL BRANDS LLC
Category: otc | Type: HUMAN OTC DRUG LABEL
Date: 20231111

ACTIVE INGREDIENTS: OCTISALATE 50 mg/1 mL; ZINC OXIDE 40 mg/1 mL
INACTIVE INGREDIENTS: ALOE VERA LEAF; WATER; GREEN TEA LEAF; MEDIUM-CHAIN TRIGLYCERIDES; WATERMELON; DECYL GLUCOSIDE; DIMETHICONE; ETHYLHEXYLGLYCERIN; GLYCERIN; HELIANTHUS ANNUUS FLOWERING TOP; C13-14 ISOPARAFFIN; LAURETH-7; PHENOXYETHANOL; .ALPHA.-TOCOPHEROL ACETATE; TRIDECYL SALICYLATE

BRICKELL Daily Defense Face Moisturizer SPF-20

Active Ingredients

Octisalate 5.00%

Zinc Oxide 4.00%

Purpose

Sunscreen

Uses

- Helps prevent sunburn
- If used as directed with other sun protection measure (see directions), decreases the risk of skin cancer and early skin aging caused by the sun.

Warnings

For external ues only.

Do not use

on damaged or broken skin.

When using this product

keep out of eyes. Rinse with water to remove.

Stop use and consult physician

if irritation or rash develops.

Keep out of reach of children.

If product is swallowed, get medical attention or contact poison control center immediately.

Directions

Apply liberally 15-minutes before sun exposure.

Reapply:

At least every two hours Immediately after swimming, sweating or towel drying.

SUN PROTECTION MEASURES: Spending time in the sun increases your risk of skin cancer and early skin aging. To decrease this risk, regularly use suncreen with broad spectrum protection and an SPF rating of 15 or higher, along with other sun protection measures including:

Limit time in the sun, especially between 10 am and 2pm.

Wear long sleeve shirts, pants, hats and sunglasses.

For children under 6-months, consult a physician.

Other Ingredients

Aloe Barbadensis Leaf (Aloe Vera Gel) Juice, Aqua (Deionized Water), Camellia Sinensis (Green Tea) Extract, Caprylic/Capric Triglyceride, Citrullus Lanatus (Watermelon) Extract, Decyl Glucoside, Dimethicone, Ethylhexylglycerin, Glycerin, Helianthus Annuus (Sunflower) Oil, C13-14 Isoparaffin, Laureth-7, Phenoxyethanol, Polyacrylamide, Tocopheryl Acetate (Vitamin E), Tridecyl Salicylate.